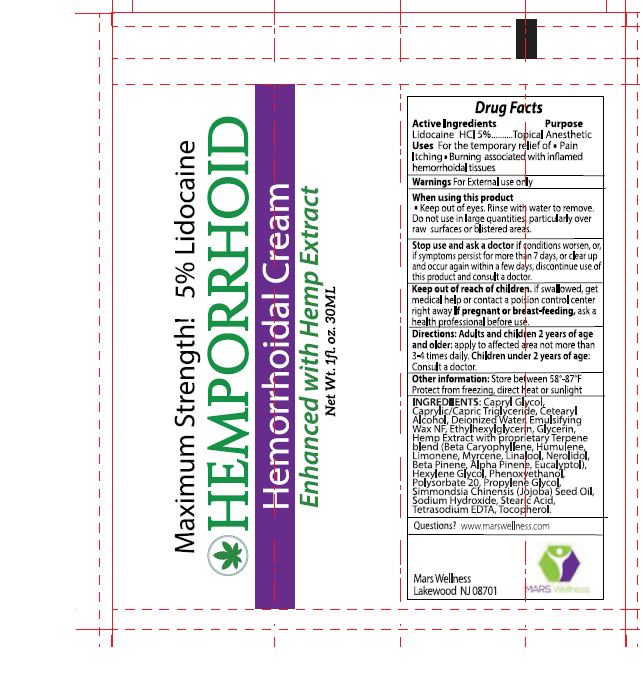 DRUG LABEL: Hemporrhoid
NDC: 76348-590 | Form: CREAM
Manufacturer: Renu Laboratories, Inc.
Category: otc | Type: HUMAN OTC DRUG LABEL
Date: 20220114

ACTIVE INGREDIENTS: LIDOCAINE HYDROCHLORIDE 1.4 g/28 g
INACTIVE INGREDIENTS: CARYOPHYLLENE; .BETA.-PINENE; STEARIC ACID; CAPRYLYL GLYCOL; CETOSTEARYL ALCOHOL; WHITE WAX; HUMULENE; MYRCENE; LINALOOL, (+)-; EDETATE SODIUM; CANNABIDIOL; EUCALYPTOL; PHENOXYETHANOL; SODIUM HYDROXIDE; HEXYLENE GLYCOL; .ALPHA.-PINENE; NEROLIDOL; PROPYLENE GLYCOL; CANNABIS SATIVA SEED OIL; TOCOPHEROL; LIMONENE, (+)-; MEDIUM-CHAIN TRIGLYCERIDES; ETHYLHEXYLGLYCERIN; JOJOBA OIL; WATER; GLYCERIN; POLYSORBATE 20

HEMPORRHOID CREAM

STATEMENT OF IDENTITY

Hemorrhoidal Cream

ACTIVE INGREDIENT

Lidocaine HCl 5%

PURPOSE

Topical Anesthetic

Uses

For the temporary relief of

- Pain
- Itching
- Burning associated with inflamed hemorrhoidal tissues

WARNINGS

For external use only

When using this product

- Keep out of eyes. Rinse with water to remove. Do not use in large quantities, particularly over raw surfaces or blistered areas.

Stop use and ask a doctor if conditions worsen, or, if symptoms persist for more than 7 days, or clear up and occur again within a few days. Discontinue use of this product and consult a doctor.

Keep out of reach of children. If swallowed, get medical help or contact a poison control center right away.

PREGNANCY OR BREAST FEEDING

If pregnant or breast-feeding, ask a health professional before use.

Directions:

Adults and children 2 years of age and older: apply to affected area not more than 3 - 4 times daily.

Children under 2 years of age: Consult a doctor.

Other information: Store between 58 - 87° F

Protect from freezing, direct heat or sunlight.

Questions? www.marswellness.com

Mars Wellness

Lakewood, NJ 08701

INACTIVE INGREDIENT

INGREDIENTS: Capryl Glycol, Caprylic / Capric Triglyceride, Cetearyl Alcohol, Deionized Water, Emulsifying Wax NF, Ethylhexylglycerin, Glycerin, Hemp Extract with proprietary Terpene blend: (Beta Caryophyllene, Humulene, Limonene, Myrcene, Linalool, Nerolidol, Beta Pinene, Alpha Pinene, Eucalyptol), Hexylene Glycol, Phenoxyethanol, Polysorbate 20, Propylene Glycol, Simmondsia Chinensis (Jojoba) Seed Oil, Sodium Hydroxide, Stearic Acid, Tetrasodium EDTA, Tocopherol.

PACKAGE LABEL

HEMPORRHOID TUBE ART